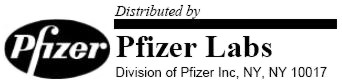 DRUG LABEL: Unknown
Manufacturer: Pfizer Labs
Category: prescription | Type: HUMAN PRESCRIPTION DRUG LABELING
Date: 20051207

TERRAMYCIN®
oxytetracycline
hydrochloride
CAPSULES

DESCRIPTION

Oxytetracycline is a product of the metabolism of Streptomyces rimosus and is one of the family of tetracycline antibiotics. A 1 percent solution in water is acidic (pH about 2.5). Its potency is affected in solutions more acid than pH 2 and it is rapidly destroyed by alkali hydroxides.

Oxytetracycline diffuses readily through the placenta into the fetal circulation, into the pleural fluid and, under some circumstances, into the cerebrospinal fluid. It appears to be concentrated in the hepatic system and excreted in the bile, so that it appears in the feces, as well as in the urine, in a biologically active form.

Inert ingredients in the formulation are: glucosamine hydrochloride; hard gelatin capsules (which may contain Red 3, Yellow 10 and other inert ingredients); magnesium stearate; sodium lauryl sulfate; starch.

ACTIONS

Oxytetracycline is primarily bacteriostatic and is thought to exert its antimicrobial effect by the inhibition of protein synthesis. Oxytetracycline is active against a wide range of gram-negative and gram-positive organisms.

The drugs in the tetracycline class have closely similar antimicrobial spectra, and cross resistance among them is common. Microorganisms may be considered susceptible if the M.I.C. (minimum inhibitory concentration) is not more than 4.0 mcg/ml and intermediate if the M.I.C. is 4.0 to 12.5 mcg/ml.

Susceptibility plate testing: A tetracycline disc may be used to determine microbial susceptibility to drugs in the tetracycline class. If the Kirby-Bauer method of disc susceptibility testing is used, a 30 mcg tetracycline disc should give a zone of at least 19 mm when tested against a tetracycline-susceptible bacterial strain.

Tetracyclines are readily absorbed and are bound to plasma proteins in varying degree. They are concentrated by the liver in the bile, and excreted in the urine and feces at high concentrations and in a biologically active form.

INDICATIONS

Oxytetracycline is indicated in infections caused by the following microorganisms:

- Rickettsiae (Rocky Mountain spotted fever, typhus fever and the typhus group, Q fever, rickettsialpox and tick fevers),
- Mycoplasma pneumoniae (PPLO, Eaton Agent),
- Agents of psittacosis and ornithosis,
- Agents of lymphogranuloma venereum and granuloma inguinale,
- The spirochetal agent of relapsing fever (Borrelia recurrentis).

The following gram negative microorganisms:

- Haemophilus ducreyi (chancroid),
- Pasteurella pestis, and Pasteurella tularensis,
- Bartonella bacilliformis,
- Bacteroides species,
- Vibrio comma and Vibrio fetus,
- Brucella species (in conjunction with streptomycin).

Because many strains of the following groups of microorganisms have been shown to be resistant to tetracyclines, culture and susceptibility testing are recommended.

Oxytetracycline is indicated for treatment of infections caused by the following gram-negative microorganisms, when bacteriologic testing indicates appropriate susceptibility to the drug:

- Escherichia coli,
- Enterobacter aerogenes (formerly Aerobacter aerogenes),
- Shigella species,
- Mima species and Herellea species,
- Haemophilus influenzae (respiratory infections),
- Klebsiella species (respiratory and urinary infections).

Oxytetracycline is indicated for treatment of infections caused by the following gram-positive microorganisms when bacteriologic testing indicates appropriate susceptibility to the drug:

Streptococcus species:

Up to 44 percent of strains of Streptococcus pyogenes and 74 percent of Streptococcus faecalis have been found to be resistant to tetracycline drugs. Therefore, tetracyclines should not be used for streptococcal disease unless the organism has been demonstrated to be sensitive.

For upper respiratory infections due to Group A beta-hemolytic streptococci, penicillin is the usual drug of choice, including prophylaxis of rheumatic fever.

Diplococcus pneumoniae,

Staphylococcus aureus, skin and soft-tissue infections. Oxytetracycline is not the drug of choice in the treatment of any type of staphylococcal infections.

When penicillin is contraindicated, tetracyclines are alternative drugs in the treatment of infections due to:

- Neisseria gonorrhoeae,
- Treponema pallidum and Treponema pertenue (syphilis and yaws),
- Listeria monocytogenes,
- Clostridium species,
- Bacillus anthracis,
- Fusobacterium fusiforme (Vincent's infection),
- Actinomyces species.

In acute intestinal amebiasis, the tetracyclines may be a useful adjunct to amebicides.

In severe acne, the tetracyclines may be useful adjunctive therapy.

Tetracyclines are indicated in the treatment of trachoma, although the infectious agent is not always eliminated, as judged by immunofluorescence.

Inclusion conjunctivitis may be treated with oral tetracyclines or with a combination of oral and topical agents.

CONTRAINDICATIONS

This drug is contraindicated in persons who have shown hypersensitivity to any of the tetracyclines.

WARNINGS

THE USE OF DRUGS OF THE TETRACYCLINE CLASS DURING TOOTH DEVELOPMENT (LAST HALF OF PREGNANCY, INFANCY, AND CHILDHOOD TO THE AGE OF 8 YEARS) MAY CAUSE PERMANENT DISCOLORATION OF THE TEETH (YELLOW-GRAY-BROWN). This adverse reaction is more common during long term use of the drugs but has been observed following repeated short term courses. Enamel hypoplasia has also been reported. TETRACYCLINE DRUGS, THEREFORE, SHOULD NOT BE USED IN THIS AGE GROUP UNLESS OTHER DRUGS ARE NOT LIKELY TO BE EFFECTIVE OR ARE CONTRAINDICATED.

If renal impairment exists, even usual oral or parenteral doses may lead to excessive systemic accumulation of the drug and possible liver toxicity. Under such conditions, lower than usual total doses are indicated and, if therapy is prolonged, serum level determinations of the drug may be advisable.

Photosensitivity manifested by an exaggerated sunburn reaction has been observed in some individuals taking tetracyclines. Patients apt to be exposed to direct sunlight or ultraviolet light should be advised that this reaction can occur with tetracycline drugs, and treatment should be discontinued at the first evidence of skin erythema.

The antianabolic action of the tetracyclines may cause an increase in BUN. While this is not a problem in those with normal renal function, in patients with significantly impaired function, higher serum levels of tetracycline may lead to azotemia, hyperphosphatemia, and acidosis.

Usage in pregnancy: (See above WARNINGS about use during tooth development.)

Results of animal studies indicate that tetracyclines cross the placenta, are found in fetal tissues and can have toxic effects on the developing fetus (often related to retardation of skeletal development). Evidence of embryotoxicity has also been noted in animals treated early in pregnancy.

Usage in newborns, infants, and children. (See above WARNINGS about use during tooth development.)

All tetracyclines form a stable calcium complex in any bone forming tissue. A decrease in the fibula growth rate has been observed in prematures given oral tetracycline in doses of 25 mg/kg every 6 hours. This reaction was shown to be reversible when the drug was discontinued.

Tetracyclines are present in the milk of lactating women who are taking a drug in this class.

PRECAUTIONS

As with other antibiotic preparations, use of this drug may result in overgrowth of nonsusceptible organisms, including fungi. If superinfection occurs, the antibiotic should be discontinued and appropriate therapy instituted.

In venereal diseases when coexistent syphilis is suspected, a dark field examination should be done before treatment is started and the blood serology repeated monthly for at least 4 months.

Because tetracyclines have been shown to depress plasma prothrombin activity, patients who are on anticoagulant therapy may require downward adjustment of their anticoagulant dosage.

In long term therapy, periodic laboratory evaluation of organ systems, including hematopoietic, renal and hepatic studies should be performed.

All infections due to Group A beta-hemolytic streptococci should be treated for at least 10 days.

Since bacteriostatic drugs may interfere with the bactericidal action of penicillin, it is advisable to avoid giving tetracycline in conjunction with penicillin.

ADVERSE REACTIONS

Gastrointestinal: anorexia, nausea, vomiting, diarrhea, glossitis, dysphagia, enterocolitis, and inflammatory lesions (with monilial overgrowth) in the anogenital region. These reactions have been caused by both the oral and parenteral administration of tetracyclines. Rare instances of esophagitis and esophageal ulcerations have been reported in patients receiving capsule and tablet forms of drugs in the tetracycline class. Most of these patients took medications immediately before going to bed. (See DOSAGE AND ADMINISTRATION.)

Skin: maculopapular and erythematous rashes. Exfoliative dermatitis has been reported but is uncommon. Photosensitivity is discussed above. (See WARNINGS.)

Renal toxicity: Rise in BUN has been reported and is apparently dose related. (See WARNINGS.)

Hypersensitivity reactions: Urticaria, angioneurotic edema, anaphylaxis, anaphylactoid purpura, pericarditis and exacerbation of systemic lupus erythematosus.

Bulging fontanels in infants and benign intracranial hypertension in adults have been reported in individuals receiving full therapeutic dosages. These conditions disappeared rapidly when the drug was discontinued.

Blood: Hemolytic anemia, thrombocytopenia, neutropenia and eosinophilia have been reported.

When given over prolonged periods, tetracyclines have been reported to produce brown-black microscopic discoloration of thyroid glands. No abnormalities of thyroid function studies are known to occur.

DOSAGE AND ADMINISTRATION

Adults: Usual daily dose, 1–2 g divided in four equal doses, depending on the severity of the infection.

For children above eight years of age: Usual daily dose, 10–20 mg per pound (25–50 mg/kg) of body weight divided in four equal doses.

Therapy should be continued for at least 24–48 hours after symptoms and fever have subsided.

For treatment of brucellosis, 500 mg oxytetracycline four times daily for 3 weeks should be accompanied by streptomycin, 1 gram intramuscularly twice daily the first week, and once daily the second week.

For treatment of uncomplicated gonorrhea, when penicillin is contraindicated, tetracycline may be used for the treatment of both males and females in the following divided dosage schedule: 1.5 grams initially followed by 0.5 gram q.i.d. for a total of 9.0 grams.

For treatment of syphilis, a total of 30–40 grams in equally divided doses over a period of 10–15 days should be given. Close follow-up, including laboratory tests, is recommended.

Administration of adequate amounts of fluid along with capsule and tablet forms of drugs in the tetracycline class is recommended to wash down the drugs and reduce the risk of esophageal irritation and ulceration. (See ADVERSE REACTIONS.)

Concomitant therapy: Antacids containing aluminum, calcium, or magnesium impair absorption and should not be given to patients taking oral tetracyclines.

Food and some dairy products also interfere with absorption. Oral forms of tetracyclines should be given 1 hour before or 2 hours after meals. Pediatric oral dosage forms should not be given with milk formulas and should be given at least 1 hour prior to feeding.

In patients with renal impairment (See WARNINGS.) Total dosage should be decreased by reduction of recommended individual doses and/or by extending time intervals between doses.

In the treatment of streptococcal infections, a therapeutic dose of oxytetracycline should be administered for at least 10 days.

HOW SUPPLIED

Terramycin (oxytetracycline HCl) Capsules are available as opaque, yellow, hard gelatin capsules which contain oxytetracycline HCl equivalent to 250 mg of oxytetracycline, and glucosamine hydrochloride: bottles of 100 (NDC 0069-0730-66), 500 (NDC 0069-0730-73).

Rx only

69-0755-32-7

March 1987